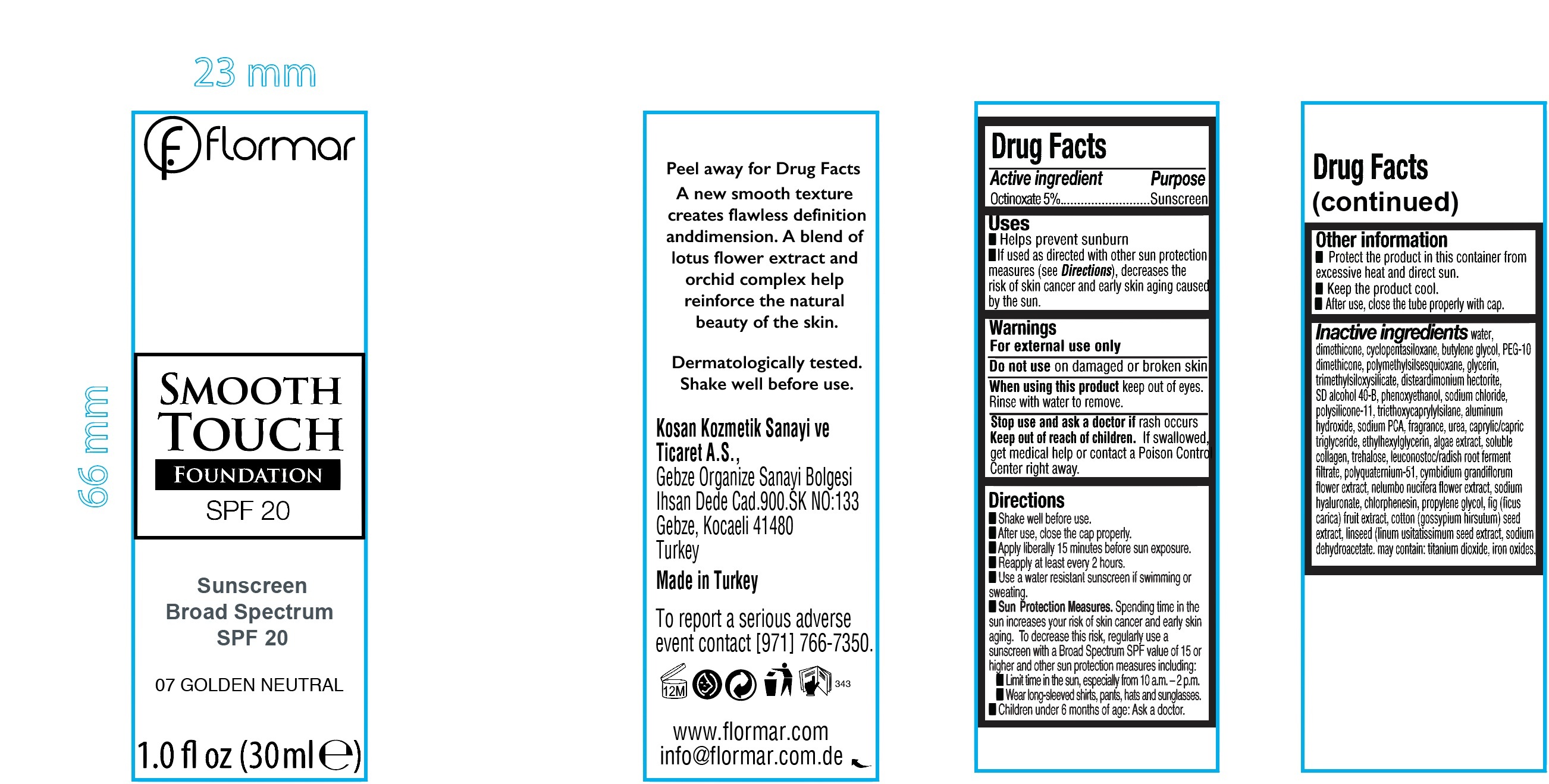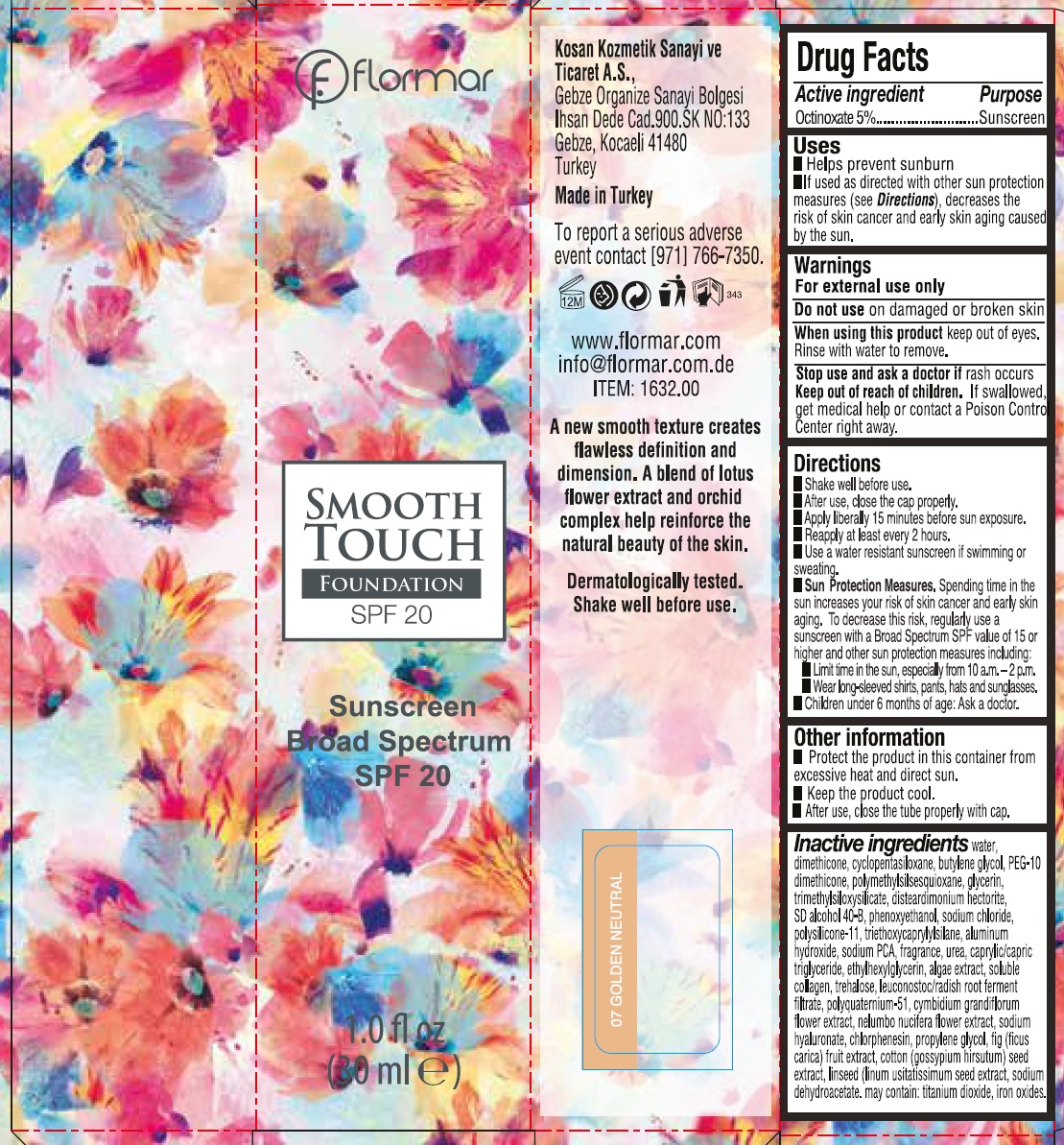 DRUG LABEL: Flormar Smooth Touch Foundation 07 Golden Neutral
NDC: 61722-276 | Form: AEROSOL
Manufacturer: Kosan Kozmetik Sanayi ve Ticaret A.S.
Category: otc | Type: HUMAN OTC DRUG LABEL
Date: 20200128

ACTIVE INGREDIENTS: OCTINOXATE 50 mg/1 mL
INACTIVE INGREDIENTS: WATER; DIMETHICONE; CYCLOMETHICONE 5; BUTYLENE GLYCOL; GLYCERIN; DISTEARDIMONIUM HECTORITE; PHENOXYETHANOL; SODIUM CHLORIDE; DIMETHICONE/VINYL DIMETHICONE CROSSPOLYMER (SOFT PARTICLE); TRIETHOXYCAPRYLYLSILANE; ALUMINUM HYDROXIDE; SODIUM PYRROLIDONE CARBOXYLATE; UREA; MEDIUM-CHAIN TRIGLYCERIDES; ETHYLHEXYLGLYCERIN; TREHALOSE; LEUCONOSTOC/RADISH ROOT FERMENT FILTRATE; CYMBIDIUM HOOKERIANUM FLOWER; NELUMBO NUCIFERA FLOWER; HYALURONATE SODIUM; CHLORPHENESIN; PROPYLENE GLYCOL; FIG; SODIUM DEHYDROACETATE; TITANIUM DIOXIDE; FERRIC OXIDE RED

Flormar Smooth Touch Foundation 07 Golden Neutral

Active ingredient

Octinoxate 5%

Purpose

Sunscreen

Uses

- Helps prevent sunburn
- If used as directed with other sun protection measures (see Directions), decreases the risk of skin cancer and early skin aging caused by the sun.

Warnings

For external use only

Do not use

on damaged or broken skin

When using this product

keep out of eyes. Rinse with water to remove.

Stop use and ask a doctor if

rash occurs

Keep out of reach of children.

If swallowed, get medical help or contact a Poison Control Center right away.

Directions

- Shake well before use.
- After use, close the cap properly.
- Apply liberally 15 minutes before sun exposure.
- Reapply at least every 2 hours.
- Use a water resistant sunscreen if swimming or sweating.
- Sun Protection Measures. Spending time in the sun increases your risk if skin cancer and early skin aging. To decrease this risk, regularly use a sunscreen with a Broad Spectrum SPF value of 15 or higher and other sun protection measures including:
- Limit time in the sun, especially from 10 a.m. -2 p.m.
- Wear long-sleeved shirts, pants, hats and sunglasses.
- Children under 6 months of age: Ask a doctor.

Other information

- Protect the product in this container from excessive heat and direct sun.
- Keep the product cool.
- After use, close the tube properly with cap.

Inactive ingredients

water, dimethicone, cyclopentasiloxane, butylene glycol, PEG-10 dimethicone, polymethylsilsesquioxane, glycerin, trimethylsiloxysilicate, disteardimonium hectorite, SD alcohol 40-B, phenoxyethanol, sodium chloride, polysilicone-11, triethoxycaprylylsilane, aluminum hydroxide, sodium PCA, fragrance, urea, caprylic/capric triglyceride, ethylhexylglycerin, algae extract, soluble collagen, trehalose, leuconostoc/radish root ferment filtrate, polyquaternium-51, cymbidium grandiflorum flower extract, nelumbo nucifera flower extract, sodium hyaluronate, chlorphenesin, propylene glycol, fig (ficus carica) fruit extract, cotton (gossypium hirsutum) seed extract, linseed (linum usitatissimum seed extract, sodium dehydroacetate. may contain: titanium dioxide, iron oxides.